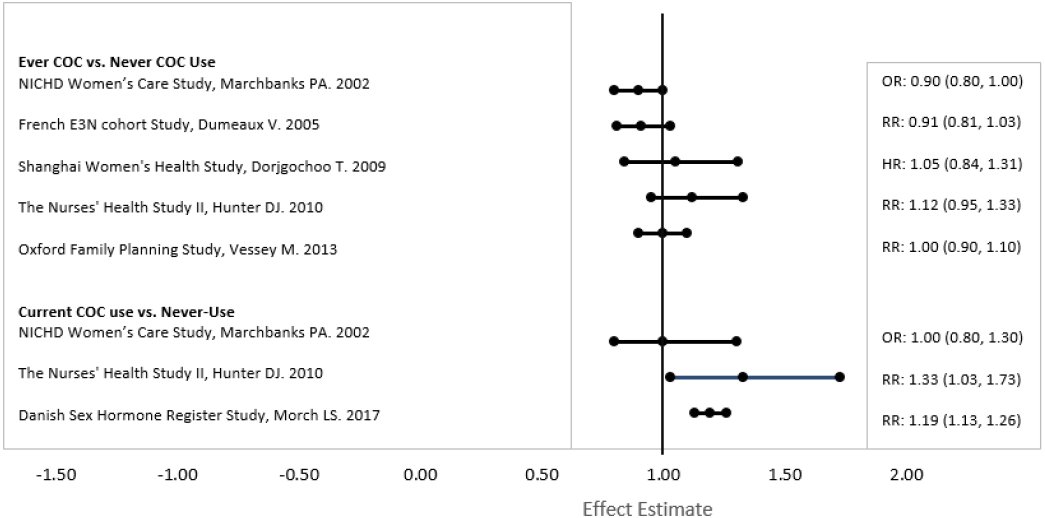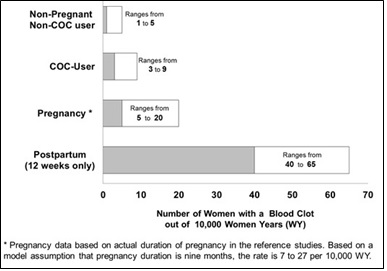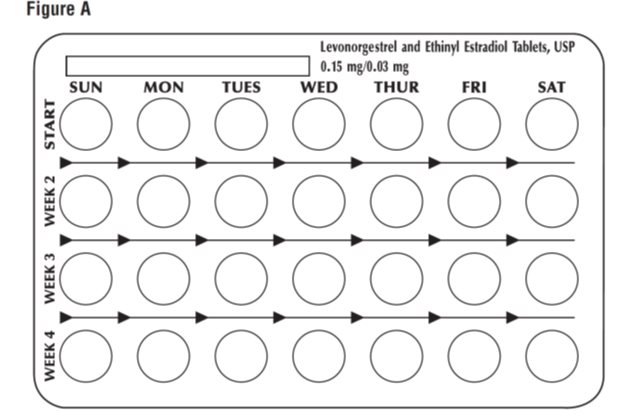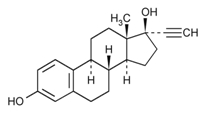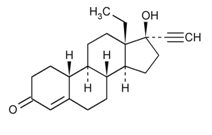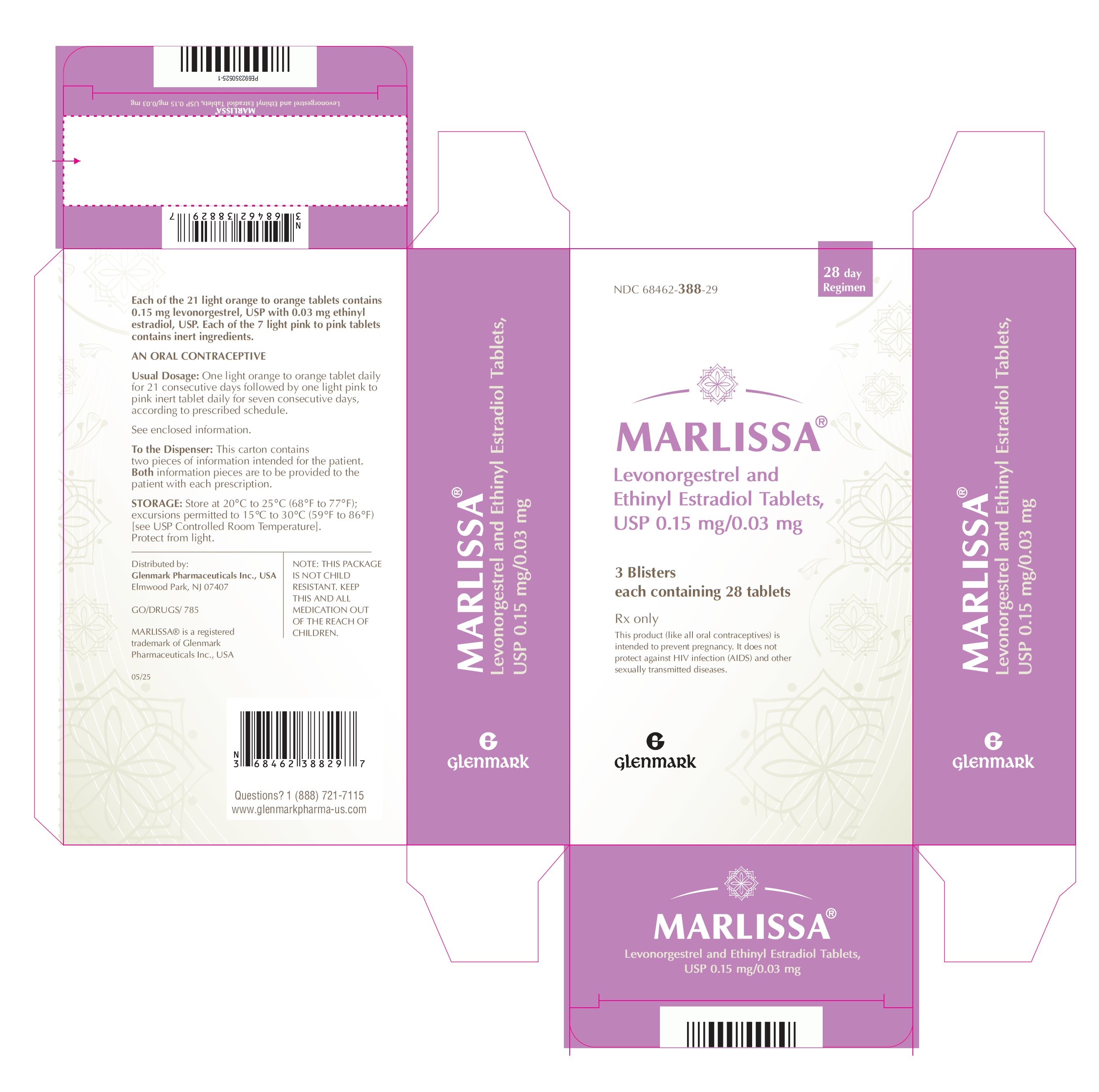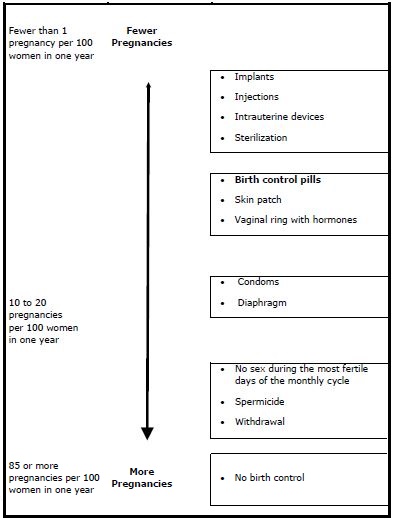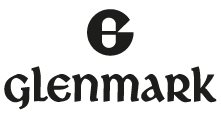 DRUG LABEL: MARLISSA
NDC: 68462-388 | Form: KIT | Route: ORAL
Manufacturer: Glenmark Pharmaceuticals Inc., USA
Category: prescription | Type: HUMAN PRESCRIPTION DRUG LABEL
Date: 20260129

ACTIVE INGREDIENTS: LEVONORGESTREL 0.15 mg/1 1; ETHINYL ESTRADIOL 0.03 mg/1 1
INACTIVE INGREDIENTS: FD&C YELLOW NO. 6; LACTOSE MONOHYDRATE; MAGNESIUM STEARATE; POLACRILIN POTASSIUM; MICROCRYSTALLINE CELLULOSE; POVIDONE, UNSPECIFIED; TALC; D&C RED NO. 30; LACTOSE MONOHYDRATE; MAGNESIUM STEARATE; POLACRILIN POTASSIUM; MICROCRYSTALLINE CELLULOSE; POVIDONE, UNSPECIFIED; TALC

MARLISSA®
(Levonorgestrel and Ethinyl Estradiol Tablets, USP 0.15 mg/0.03 mg)

WARNING: CIGARETTE SMOKING AND SERIOUS CARDIOVASCULAR EVENTS

Cigarette smoking increases the risk of serious cardiovascular events from combination oral contraceptive (COC) use. This risk increases with age, particularly in women over 35 years of age, and with the number of cigarettes smoked. For this reason, COCs, including MARLISSA®, are contraindicated in women who are over 35 years of age and smoke [see CONTRAINDICATIONS and WARNINGS (1)].

DESCRIPTION

MARLISSA® (levonorgestrel and ethinyl estradiol tablets) is a combination oral contraceptive (COC) consisting of 21 light orange to orange color MARLISSA® (levonorgestrel and ethinyl estradiol tablets), each containing 0.15 mg of levonorgestrel, USP, a totally synthetic progestogen, and 0.03 mg of ethinyl estradiol, USP, an estrogen and 7 light pink to pink inert tablets (without hormones).

The structural formulas for the active components are:

Levonorgestrel, USP

C21H28O2 MW: 312.4

Levonorgestrel, USP is chemically d(-)-13-Ethyl-17-hydroxy-18,19-dinor-17α-pregn-4-en-20-yn-3-one

Ethinyl Estradiol, USP

C20H24O2 MW: 296.4

Ethinyl Estradiol, USP is 19-nor-17α-pregna-1,3,5(10)-trien-20-yne-3, 17-diol.

Each light orange to orange color active tablet contains the following inactive ingredients: FD&C Yellow no. 6, lactose monohydrate, magnesium stearate, microcrystalline cellulose, polacrilin potassium, povidone and talc. In addition, the film-coating contains hypromellose and macrogol.

Each light pink to pink inert tablet contains the following inactive ingredients: D&C Red no. 30, lactose monohydrate, magnesium stearate, microcrystalline cellulose, polacrilin potassium, povidone and talc.

CLINICAL PHARMACOLOGY

Combination oral contraceptives prevent pregnancy primarily by suppressing ovulation.

INDICATIONS AND USAGE

MARLISSA® (levonorgestrel and ethinyl estradiol tablets) is indicated for use by females of reproductive potential to prevent pregnancy.

CONTRAINDICATIONS

MARLISSA® (levonorgestrel and ethinyl estradiol tablets) is contraindicated in females who are known to have the following conditions:

- A high risk of arterial or venous thrombotic diseases. Examples include women who are known to:
  - Smoke, if over age 35 [see BOXED WARNING and WARNINGS (1)].
  - Have current or history of deep vein thrombosis or pulmonary embolism [see WARNINGS (1)].
  - Have cerebrovascular disease [see WARNINGS (1)].
  - Have coronary artery disease [see WARNINGS (1)].
  - Have thrombogenic valvular or thrombogenic rhythm diseases of the heart (for example, subacute bacterial endocarditis with valvular disease, or atrial fibrillation) [see WARNINGS (1)].
  - Have inherited or acquired hypercoagulopathies [see WARNINGS (1)].
  - Have uncontrolled hypertension or hypertension with vascular disease [see WARNINGS (3)].
  - Have diabetes mellitus and are over age 35, diabetes mellitus with hypertension or vascular disease or other end-organ damage, or diabetes mellitus of >20 years duration [see WARNINGS (7)].
  - Have headaches with focal neurological symptoms, migraine headaches with aura, or over age 35 with any migraine headaches [see WARNINGS (8)].
- Current diagnosis of, or history of, breast cancer, which may be hormone-sensitive.
- Liver tumors, acute viral hepatitis, or severe (decompensated) cirrhosis [see WARNINGS (2)].
- Use of Hepatitis C drug combinations containing ombitasvir/paritaprevir/ritonavir, with or without dasabuvir, due to the potential for ALT elevations [see WARNINGS (5)].
- Undiagnosed abnormal uterine bleeding [see WARNINGS (9)].

WARNINGS

1. Thromboembolic Disorders and Other Vascular Conditions

- Stop MARLISSA® (levonorgestrel and ethinyl estradiol tablets) if an arterial or venous thrombotic/thromboembolic event occurs.
- Stop MARLISSA® (levonorgestrel and ethinyl estradiol tablets) if there is unexplained loss of vision, proptosis, diplopia, papilledema, or retinal vascular lesions and evaluate for retinal vein thrombosis immediately.
- Discontinue MARLISSA® (levonorgestrel and ethinyl estradiol tablets) during prolonged immobilization. If feasible, stop MARLISSA® at least four weeks before and through two weeks after major surgery, or other surgeries known to have an elevated risk of thromboembolism.
- Start MARLISSA® (levonorgestrel and ethinyl estradiol tablets) no earlier than four weeks after delivery in females who are not breastfeeding. The risk of postpartum thromboembolism decreases after the third postpartum week, whereas the likelihood of ovulation increases after the third postpartum week.
- Before starting MARLISSA® (levonorgestrel and ethinyl estradiol tablets) evaluate any past medical history or family history of thrombotic or thromboembolic disorders and consider whether the history suggests an inherited or acquired hypercoagulopathy. MARLISSA® (levonorgestrel and ethinyl estradiol tablets) is contraindicated in females with a high risk of arterial or venous thrombotic/thromboembolic diseases (see CONTRAINDICATIONS).

Arterial Events

COCs increase the risk of cardiovascular events and cerebrovascular events, such as myocardial infarction and stroke. The risk is greater among older women (> 35 years of age), smokers, and females with hypertension, dyslipidemia, diabetes, or obesity.

MARLISSA® (levonorgestrel and ethinyl estradiol tablets) is contraindicated in women over 35 years of age who smoke (see CONTRAINDICATIONS). Cigarette smoking increases the risk of serious cardiovascular events from COC use. This risk increases with age, particularly in women over 35 years of age, and with the number of cigarettes smoked.

Venous Events

Use of COCs increases the risk of venous thromboembolic events (VTEs), such as deep vein thrombosis and pulmonary embolism. Risk factors for VTEs include smoking, obesity, and family history of VTE, in addition to other factors that contraindicate use of COCs (see CONTRAINDICATIONS). While the increased risk of VTE associated with use of COCs is well-established, the rates of VTE are even greater during pregnancy, and especially during the postpartum period (see Figure 1). The rate of VTE in females using COCs has been estimated to be 3 to 9 cases per 10,000 woman-years.

The risk of VTE is highest during the first year of use of a COC and when restarting hormonal contraception after a break of four weeks or longer. Based on results from a few studies, there is some evidence that this is true for non-oral products as well. The risk of thromboembolic disease due to COCs gradually disappears after COC use is discontinued.

Figure 1 shows the risk of developing a VTE for females who are not pregnant and do not use oral contraceptives, for females who use oral contraceptives, for pregnant females, and for females in the postpartum period. To put the risk of developing a VTE into perspective: If 10,000 females who are not pregnant and do not use oral contraceptives are followed for one year, between 1 and 5 of these females will develop a VTE.

Figure 1: Likelihood of Developing a VTE

2. Liver Disease

Elevated Liver Enzymes

MARLISSA® (levonorgestrel and ethinyl estradiol tablets) is contraindicated in females with acute viral hepatitis or severe (decompensated) cirrhosis of liver (see CONTRAINDICATIONS). Discontinue MARLISSA® if jaundice develops. Acute liver test abnormalities may necessitate the discontinuation of COC use until the liver tests return to normal and COC causation has been excluded.

Liver Tumors

MARLISSA® (levonorgestrel and ethinyl estradiol tablets) is contraindicated in females with benign or malignant liver tumors (see CONTRAINDICATIONS). COCs increase the risk of hepatic adenomas. An estimate of the attributable risk is 3.3 cases/100,000 COC users. Rupture of hepatic adenomas may cause death from abdominal hemorrhage.

Studies have shown an increased risk of developing hepatocellular carcinoma in long-term (> 8 years) COC users. The attributable risk of liver cancers in COC users is less than one case per million users.

3. Hypertension

MARLISSA® (levonorgestrel and ethinyl estradiol tablets) is contraindicated in females with uncontrolled hypertension or hypertension with vascular disease (see CONTRAINDICATIONS). For all females, including those with well- controlled hypertension, monitor blood pressure at routine visits and stop MARLISSA® if blood pressure rises significantly.

An increase in blood pressure has been reported in females using COCs, and this increase is more likely in older women with extended duration of use. The effect of COCs on blood pressure may vary according to the progestin in the COC.

4. Age-related Considerations

The risk for cardiovascular disease and prevalence of risk factors for cardiovascular disease increase with age. Certain conditions, such as smoking and migraine headache without aura, that do not contraindicate COC use in younger females, are contraindications to use in women over 35 years of age [see CONTRAINDICATIONS and WARNINGS (1)]. Consider the presence of underlying risk factors that may increase the risk of cardiovascular disease or VTE, particularly before initiating a COC for women over 35 years, such as:

- Hypertension
- Diabetes
- Dyslipidemia
- Obesity

5. Risk of Liver Enzyme Elevations with Concomitant Hepatitis C Treatment

During clinical trials with the Hepatitis C combination drug regimen that contains ombitasvir/paritaprevir/ritonavir, with or without dasabuvir, ALT elevations greater than 5 times the upper limit of normal (ULN), including some cases greater than 20 times the ULN, were significantly more frequent in women using ethinyl estradiol-containing medications such as COCs. Discontinue MARLISSA® (levonorgestrel and ethinyl estradiol tablets) prior to starting therapy with the combination drug regimen ombitasvir/paritaprevir/ritonavir, with or without dasabuvir (see CONTRAINDICATIONS).

MARLISSA® (levonorgestrel and ethinyl estradiol tablets) can be restarted approximately 2 weeks following completion of treatment with the combination drug regimen.

6. Gallbladder Disease

Studies suggest an increased risk of developing gallbladder disease among COC users. Use of COCs may also worsen existing gallbladder disease.

A past history of COC-related cholestasis predicts an increased risk with subsequent COC use. Females with a history of pregnancy-related cholestasis may be at an increased risk for COC- related cholestasis.

7. Adverse Carbohydrate and Lipid Metabolic Effects

Hyperglycemia

MARLISSA® (levonorgestrel and ethinyl estradiol tablets) is contraindicated in diabetic women over age 35, or females who have diabetes with hypertension, nephropathy, retinopathy, neuropathy, other vascular disease, or females with diabetes of > 20 years duration (see CONTRAINDICATIONS). MARLISSA® may decrease glucose tolerance. Carefully monitor prediabetic and diabetic females who are using MARLISSA®.

Dyslipidemia

Consider alternative contraception for females with uncontrolled dyslipidemia. MARLISSA® (levonorgestrel and ethinyl estradiol tablets) may cause adverse lipid changes.

Females with hypertriglyceridemia, or a family history thereof, may have an increase in serum triglyceride concentrations when using MARLISSA®, which may increase the risk of pancreatitis.

8. Headache

MARLISSA® (levonorgestrel and ethinyl estradiol tablets) is contraindicated in females who have headaches with focal neurological symptoms or have migraine headaches with aura, and in women over age 35 years who have migraine headaches with or without aura (see CONTRAINDICATIONS).

If a woman using MARLISSA® (levonorgestrel and ethinyl estradiol tablets) develops new headaches that are recurrent, persistent, or severe, evaluate the cause and discontinue MARLISSA® if indicated. Consider discontinuation of MARLISSA® if there is an increased frequency or severity of migraines during COC use (which may be prodromal of a cerebrovascular event).

9. Bleeding Irregularities and Amenorrhea

Unscheduled Bleeding and Spotting

Females using MARLISSA® (levonorgestrel and ethinyl estradiol tablets) may experience unscheduled (breakthrough or intracyclic) bleeding and spotting, especially during the first three months of use. Bleeding irregularities may resolve over time or by changing to a different contraceptive product. If bleeding persists or occurs after previously regular cycles, evaluate for causes such as pregnancy or malignancy.

In two clinical trials of MARLISSA® (levonorgestrel and ethinyl estradiol) (1084 subjects reporting for a total of 8186 treatment cycles and 238 subjects reporting for a total of 1102 treatment cycles), breakthrough bleeding occurred in 6.9% and 8.1% of reported cycles, and spotting occurred in 8.6% and 7.9% of reported cycles over the total study duration, respectively. In the two trials, intermenstrual bleeding (i.e., breakthrough bleeding and/or spotting) occurred in 13.1% and 12.9% of reported cycles over the total study duration, respectively. In one trial, 33 subjects out of 1084 (3%) discontinued due to bleeding irregularities (i.e., breakthrough bleeding and spotting); in the other trial, 6 subjects out of 238 (2.5%) discontinued due to bleeding irregularities.

Amenorrhea and Oligomenorrhea

Females who use MARLISSA® (levonorgestrel and ethinyl estradiol tablets) may experience absence of scheduled (withdrawal) bleeding, even if they are not pregnant. In two clinical trials of MARLISSA®, one including 8186 reported treatment cycles, and the other including 1102 reported treatment cycles, amenorrhea occurred in 1.5% of treatment cycles in each trial.

If scheduled bleeding does not occur, consider the possibility of pregnancy. If the patient has not adhered to the prescribed dosing schedule (missed one or two active tablets or started taking them on a day later than she should have), consider the possibility of pregnancy at the time of the first missed period and perform appropriate diagnostic measures. If the patient has adhered to the prescribed dosing schedule and misses two consecutive periods, rule out pregnancy.

After discontinuation of a COC, amenorrhea or oligomenorrhea may occur, especially if these conditions were pre-existent.

10. Depression

Carefully observe females with a history of depression and discontinue MARLISSA® (levonorgestrel and ethinyl estradiol tablets) if depression recurs to a serious degree. Data on the association of COCs with onset of depression or exacerbation of existing depression are limited.

11 Malignant Neoplasms

Breast Cancer

MARLISSA® (levonorgestrel and ethinyl estradiol tablets) is contraindicated in females who currently have or have had breast cancer because breast cancer may be hormonally sensitive [see Contraindications (4)].

Epidemiology studies have not found a consistent association between use of combined oral contraceptives (COCs) and breast cancer risk. Studies do not show an association between ever (current or past) use of COCs and risk of breast cancer. However, some studies report a small increase in the risk of breast cancer among current or recent users (<6 months since last use) and current users with longer duration of COC use [see ADVERSE REACTIONS, Postmarketing Experience].

Cervical Cancer

Some studies suggest that COCs are associated with an increase in the risk of cervical cancer or intraepithelial neoplasia. There is controversy about the extent to which these findings are due to differences in sexual behavior and other factors.

12. Effect on Binding Globulins

The estrogen component of MARLISSA® (levonorgestrel and ethinyl estradiol tablets) may raise the serum concentrations of thyroxine- binding globulin, sex hormone-binding globulin, and cortisol-binding globulin. The dose of replacement thyroid hormone or cortisol therapy may need to be increased.

13. Hereditary Angioedema

In females with hereditary angioedema, exogenous estrogens may induce or exacerbate symptoms of angioedema.

14. Chloasma

Chloasma may occur with MARLISSA® (levonorgestrel and ethinyl estradiol tablets) use, especially in females with a history of chloasma gravidarum. Advise females with a history of chloasma to avoid exposure to the sun or ultraviolet radiation while using MARLISSA®.

PRECAUTIONS

1. Lipid Disorders

Women who are being treated for hyperlipidemias should be followed closely if they elect to use oral contraceptives. Some progestogens may elevate LDL levels and may render the control of hyperlipidemias more difficult [see WARNINGS (7)].

In patients with familial defects of lipoprotein metabolism receiving estrogen-containing preparations, there have been case reports of significant elevations of plasma triglycerides leading to pancreatitis.

2. Fluid Retention

Oral contraceptives may cause some degree of fluid retention. They should be prescribed with caution, and only with careful monitoring, in patients with conditions which might be aggravated by fluid retention.

3. Gastrointestinal Motility

Diarrhea and/or vomiting may reduce hormone absorption (see DOSAGE AND ADMINISTRATION).

4 Drug Interactions

The sections below provide information on substances for which data on drug interactions with COCs are available. There is little information available about the clinical effect of most drug interactions that may affect COCs. However, based on the known pharmacokinetic effects of these drugs, clinical strategies to minimize any potential adverse effect on contraceptive effectiveness or safety are suggested.

Consult the approved product labeling of all concurrently used drugs to obtain further information about interactions with COCs or the potential for metabolic enzyme or transporter system alterations.

No drug-drug interaction studies were conducted with MARLISSA® (levonorgestrel and ethinyl estradiol tablets).

4.1 Effects of Other Drugs on Combined Oral Contraceptives

Substances Decreasing the Plasma Concentrations of COCs and Potentially Diminishing the Efficacy of COCs:

Table 1 includes substances that demonstrated an important drug interaction with MARLISSA® (levonorgestrel and ethinyl estradiol tablets).

Table 1: Significant Drug Interactions Involving Substances That Affect COCs

Metabolic Enzyme Inducers
Clinical effect | - Concomitant use of COCs with metabolic enzyme inducers may decrease the plasma concentrations of the estrogen and/or progestin component of COCs. - Decreased exposure of the estrogen and/or progestin component of COCs may potentially diminish the effectiveness of COCs and may lead to contraceptive failure or an increase in breakthrough bleeding.
Prevention or management | - Counsel females to use an alternative method of contraception or a backup method when enzyme inducers are used with COCs. - Continue backup contraception for 28 days after discontinuing the enzyme inducer to maintain contraceptive reliability.
Examples | Aprepitant, barbiturates, bosentan, carbamazepine, efavirenz, felbamate, griseofulvin, oxcarbazepine, phenytoin, rifampin, rifabutin, rufinamide, topiramate, products containing St. John’s worta, and certain protease inhibitors (see separate section on protease inhibitors below).
Colesevelam
Clinical effect | - Concomitant use of COCs with colesevelam significantly decreases systemic exposure of ethinyl estradiol. - Decreased exposure of the estrogen component of COCs may potentially reduce contraceptive efficacy or result in an increase in breakthrough bleeding, depending on the strength of ethinyl estradiol in the COC.
Prevention or management | Administer 4 or more hours apart to attenuate this drug interaction.

a Induction potency of St. John’s wort may vary widely based on preparation.

Substances increasing the systemic exposure of COCs:

Co-administration of atorvastatin or rosuvastatin and COCs containing ethinyl estradiol increase systemic exposure of ethinyl estradiol by approximately 20 to 25 percent. Ascorbic acid and acetaminophen may increase systemic exposure of ethinyl estradiol, possibly by inhibition of conjugation. CYP3A inhibitors such as itraconazole, voriconazole, fluconazole, grapefruit juice, or ketoconazole may increase systemic exposure of the estrogen and/or progestin component of COCs.

Human immunodeficiency virus (HIV)/hepatitis C virus (HCV) protease inhibitors and non‑nucleoside reverse transcriptase inhibitors:

Significant decreases in systemic exposure of the estrogen and/or progestin have been noted when COCs are co-administered with some HIV protease inhibitors (e.g., nelfinavir, ritonavir, darunavir/ritonavir, (fos)amprenavir/ritonavir, lopinavir/ritonavir, and tipranavir/ritonavir), some HCV protease inhibitors (e.g., boceprevir and telaprevir), and some non-nucleoside reverse transcriptase inhibitors (e.g., nevirapine).

In contrast, significant increases in systemic exposure of the estrogen and/or progestin have been noted when COCs are co-administered with certain other HIV protease inhibitors (e.g., indinavir and atazanavir/ritonavir) and with other non-nucleoside reverse transcriptase inhibitors (e.g., etravirine).

4.2 Effects of Combined Oral Contraceptives on Other Drugs

Table 2 provides significant drug interaction information for drugs co-administered with MARLISSA® (levonorgestrel and ethinyl estradiol tablets).

Table 2: Significant Drug Interaction Information for Drugs Co-Administered With COCs

Lamotrigine
Clinical effect | - Concomitant use of COCs with lamotrigine may significantly decrease systemic exposure of lamotrigine due to induction of lamotrigine glucuronidation. - Decreased systemic exposure of lamotrigine may reduce seizure control.
Prevention or management | Dose adjustment may be necessary. Consult the approved product labeling for lamotrigine.
Thyroid Hormone Replacement Therapy or Corticosteroid Replacement Therapy
Clinical effect | Concomitant use of COCs with thyroid hormone replacement therapy or corticosteroid replacement therapy may increase systemic exposure of thyroid- binding and cortisol-binding globulin (see Warnings, EFFECT ON BINDING GLOBULINS).
Prevention or management | The dose of replacement thyroid hormone or cortisol therapy may need to be increased. Consult the approved product labeling for the therapy in use (see Warnings, EFFECT ON BINDING GLOBULINS).
Other Drugs
Clinical effect | Concomitant use of COCs may decrease systemic exposure of acetaminophen, morphine, salicylic acid, and temazepam. Concomitant use with ethinyl estradiol‑containing COCs may increase systemic exposure of other drugs (e.g., cyclosporine, prednisolone, theophylline, tizanidine, and voriconazole).
Prevention or management | The dosage of drugs that can be affected by this interaction may need to be increased. Consult the approved product labeling for the concomitantly used drug.

4.3 Concomitant Use with Hepatitis C Virus (HCV) Combination Therapy –Liver Enzyme Elevation

Do not co-administer MARLISSA® (levonorgestrel and ethinyl estradiol tablets) with HCV drug combinations containing ombitasvir/paritaprevir/ritonavir, with or without dasabuvir, [see Warnings (5)], and glecaprevir/pibrentasvir due to potential for ALT elevations.

4.4 Effect on Laboratory Tests

The use of COCs may influence the results of certain laboratory tests, such as coagulation factors, lipids, glucose tolerance, and binding proteins.

5. Carcinogenesis

See WARNINGS. (11).

6. Pregnancy

Risk Summary

Discontinue MARLISSA® (levonorgestrel and ethinyl estradiol tablets) if pregnancy occurs because there is no reason to use COCs in pregnancy. Epidemiologic studies and meta- analyses have not found an increased risk of genital or nongenital birth defects (including cardiac anomalies and limb-reduction defects) following exposure to COCs before conception or during early pregnancy. Animal studies to evaluate embryo/fetal toxicity were not conducted.

In the U.S. general population, the estimated background risk of major birth defects and miscarriage in clinically recognized pregnancies is 2 to 4 percent and 15 to 20 percent, respectively.

7. Lactation

Risk Summary

Contraceptive hormones and/or metabolites are present in human milk. COCs can reduce milk production in breastfeeding females. This reduction can occur at any time but is less likely to occur once breastfeeding is well-established. When possible, advise the nursing female to use other methods of contraception until she discontinues breastfeeding. (see DOSAGE AND ADMINISTRATION). The developmental and health benefits of breastfeeding should be considered along with the mother’s clinical need for MARLISSA® (levonorgestrel and ethinyl estradiol tablets) and any potential adverse effects on the breastfed child from MARLISSA® or from the underlying maternal condition.

8. Pediatric Use

Safety and efficacy of MARLISSA® (levonorgestrel and ethinyl estradiol tablets) have been established in females of reproductive potential. Use of MARLISSA® before menarche is not indicated.

9. Geriatric Use

MARLISSA® (levonorgestrel and ethinyl estradiol tablets) has not been studied in postmenopausal women and is not indicated in this population.

10. PATIENT COUNSELING INFORMATION

- Counsel patients that cigarette smoking increases the risk of serious cardiovascular events from COC use, and that women who are over 35 years old and smoke should not use COCs (see BOXED WARNING and CONTRAINDICATIONS).
- Counsel patients that this product does not protect against HIV-infection (AIDS) and other sexually transmitted infections.
- Counsel patients to take one tablet daily by mouth at the same time every day. Instruct patients what to do in the event pills are missed (see DOSAGE AND ADMINISTRATION).
- Counsel patients to use a back-up or alternative method of contraception when enzyme inducers are used with COCs [see PRECAUTIONS (4.1)].
- Counsel patients who are breastfeeding or who desire to breastfeed that COCs may reduce breast milk production. This is less likely to occur if breastfeeding is well established [see PRECAUTIONS (7)].
- Counsel any patient who starts MARLISSA® (levonorgestrel and ethinyl estradiol tablets) postpartum, and who has not yet had a period, to use an additional method of contraception until she has taken a light orange tablet for 7 consecutive days (see DOSAGE AND ADMINISTRATION).
- Counsel patients that amenorrhea may occur. Pregnancy should be considered in the event of amenorrhea, and should be ruled out if amenorrhea is associated with symptoms of pregnancy, such as morning sickness or unusual breast tenderness [see WARNINGS (9)].

Depression may occur. Women should contact their healthcare provider if depression occurs, including shortly after initiating the treatment [see WARNINGS (10)].

ADVERSE REACTIONS

The following serious adverse reactions with the use of COCs are discussed elsewhere in the labeling:

- Serious cardiovascular adverse events [see BOXED WARNING and WARNINGS (1)]
- Vascular events [see WARNINGS (1)]
- Liver disease [see WARNINGS (2)]
- Hypertension [see WARNINGS (3)]
- Gallbladder disease [see WARNINGS (6)]
- Carbohydrate and lipid effects [see WARNINGS (7)]
- Headache [see WARNINGS (8)]
- Carcinoma of the cervix [see WARNINGS (11)]

Adverse reactions reported by COC users and described elsewhere in the labeling are:

- Bleeding irregularities and amenorrhea [see WARNINGS (9)]
- Mood changes, including depression [see WARNINGS (10)]
- Melasma/chloasma which may persist [see WARNINGS (14)]
- Edema/fluid retention [see PRECAUTIONS (2)]
- Diminution in lactation when given immediately postpartum [see PRECAUTIONS (7)]

Post Marketing Experience

Five studies that compared breast cancer risk between ever-users (current or past use) of COCs and never-users of COCs reported no association between ever use of COCs and breast cancer risk, with effect estimates ranging from 0.90 to 1.12 (Figure 2).

Three studies compared breast cancer risk between current or recent COC users (<6 months since last use) and never users of COCs (Figure 2). One of these studies reported no association between breast cancer risk and COC use. The other two studies found an increased relative risk of 1.19 to 1.33 with current or recent use. Both of these studies found an increased risk of breast cancer with current use of longer duration, with relative risks ranging from 1.03 with less than one year of COC use to approximately 1.4 with more than 8 to 10 years of COC use.

Figure 2: Relevant Studies of Risk of Breast Cancer with Combined Oral Contraceptives

RR = relative risk; OR = odds ratio; HR = hazard ratio. “ever COC” are females with current or past COC use; “never COC use” are females that never used COCs.

The following adverse reactions have been reported in patients receiving oral contraceptives and are believed to be drug-related: Breast tenderness, pain, enlargement, secretion; Nausea, vomiting and gastrointestinal symptoms (such as abdominal pain, cramps and bloating); Change in menstrual flow; Temporary infertility after discontinuation of treatment; Change in weight or appetite (increase or decrease); Change in cervical erosion and secretion; Cholestatic jaundice; Rash (allergic); Vaginitis, including candidiasis; Change in corneal curvature (steepening); Intolerance to contact lenses; Mesenteric thrombosis; Decrease in serum folate levels; Exacerbation of systemic lupus erythematosus; Exacerbation of porphyria; Exacerbation of chorea; Aggravation of varicose veins; Anaphylactic/anaphylactoid reactions, including urticaria, angioedema, and severe reactions with respiratory and circulatory symptoms.

The following adverse reactions have been reported in users of oral contraceptives, and the association has been neither confirmed nor refuted: Congenital anomalies; Premenstrual syndrome; Cataracts; Optic neuritis, which may lead to partial or complete loss of vision; Cystitis-like syndrome; Nervousness; Dizziness; Hirsutism; Loss of scalp hair; Erythema multiforme; Erythema nodosum; Hemorrhagic eruption; Impaired renal function; Hemolytic uremic syndrome; Budd-Chiari syndrome; Acne; Changes in libido; Colitis; Sickle-cell disease; Cerebral-vascular disease with mitral valve prolapse; Lupus-like syndromes; Pancreatitis; Dysmenorrhea.

OVERDOSAGE

There have been no reports of serious adverse outcomes from overdose of COCs, including ingestion by children. Overdose may cause uterine bleeding in females and nausea.

DOSAGE AND ADMINISTRATION

1. How to Start and Take MARLISSA® (levonorgestrel and ethinyl estradiol tablets)

MARLISSA® (levonorgestrel and ethinyl estradiol tablets) is dispensed in a compact dispenser containing 28 tablets (see HOW SUPPLIED). MARLISSA® (levonorgestrel and ethinyl estradiol tablets) may be started using either a Day 1 start or a Sunday start (see Table 3). For the first cycle of a Sunday start regimen, an additional method of contraception should be used until after the first 7 consecutive days of administration.

Table 3: Instructions for Administration of MARLISSA® (levonorgestrel and ethinyl estradiol tablets)

Starting MARLISSA® (levonorgestrel and ethinyl estradiol tablets) in females with no current use of hormonal contraception | Day 1 start; - Take first tablet without regard to meals on the first day of menses - Take subsequent tablets once daily at the same time each day - Begin each subsequent pack on the same day of the week as the first cycle pack (i.e., on the day after taking the last tablet)
Starting MARLISSA® (levonorgestrel and ethinyl estradiol tablets) in females with no current use of hormonal contraception | Sunday start; - Take first tablet without regard to meals on the first Sunday after the onset of menstrual period - Take subsequent tablets once daily at the same time each day - Use additional nonhormonal contraception for the first seven days of product use - Begin each subsequent pack on the same day of the week as the first cycle pack (i.e., on the day after taking the last tablet)
Switching from another contraceptive method; - A COC | Start MARLISSA® (levonorgestrel and ethinyl estradiol tablets):; - On the day when the new pack of the previous COC would have been started
- Transdermal patch | - On the day when next application would have been scheduled
- Vaginal ring | - On the day when next insertion would have been scheduled
- Injection | - On the day when next injection would have been scheduled
- Intrauterine contraceptive | - On the day of removal
- Implant | - On the day of removal

Starting MARLISSA® (levonorgestrel and ethinyl estradiol tablets) after Abortion or Miscarriage

First-trimester

- After a first-trimester abortion or miscarriage, MARLISSA® (levonorgestrel and ethinyl estradiol tablets) may be started immediately. An additional method of contraception is not needed if MARLISSA® (levonorgestrel and ethinyl estradiol tablets) is started immediately.
- If MARLISSA® (levonorgestrel and ethinyl estradiol tablets) is not started within 5 days after termination of the pregnancy, the patient should use additional non-hormonal contraception (such as condoms or spermicide) for the first seven days of her first cycle of MARLISSA® (levonorgestrel and ethinyl estradiol tablets).

Second-trimester

- Do not start until 4 weeks after a second-trimester abortion or miscarriage, due to the increased risk of thromboembolic disease. Start MARLISSA® (levonorgestrel and ethinyl estradiol tablets) following the instructions in Table 3 for Day 1 or Sunday start. Use additional non-hormonal contraception (such as condoms or spermicide) for the first seven days of the patient’s first cycle of MARLISSA® (levonorgestrel and ethinyl estradiol tablets) (see CONTRAINDICATIONS, WARNINGS (1), PRECAUTIONS (10) and FDA-APPROVED PATIENT LABELING).

Starting MARLISSA® (levonorgestrel and ethinyl estradiol tablets) after Childbirth

- Do not start until 4 weeks after delivery, due to the increased risk of thromboembolic disease. Start contraceptive therapy with MARLISSA® (levonorgestrel and ethinyl estradiol tablets) following the instructions in Table 3 for women not currently using hormonal contraception.
- MARLISSA® (levonorgestrel and ethinyl estradiol tablets) is not recommended for use in lactating women (see PRECAUTIONS (7) and FDA-APPROVED PATIENT LABELING).
- If the woman has not yet had a period postpartum, consider the possibility of ovulation and conception occurring prior to use of MARLISSA® (levonorgestrel and ethinyl estradiol tablets) (see CONTRAINDICATIONS, WARNINGS (9), PRECAUTIONS (6) and FDA‑ APPROVED PATIENT LABELING).

2. Dosing MARLISSA® (levonorgestrel and ethinyl estradiol tablets)

Instruct patients to take one tablet by mouth at the same time every day. To achieve maximum contraceptive effectiveness, patients must take MARLISSA® (levonorgestrel and ethinyl estradiol tablets) as directed, in the order directed on the blister pack. The failure rate may increase when pills are missed or taken incorrectly.

3. Missed doses

Instruct patients about the handling of missed doses (e.g., to take single missed pills as soon as possible) and to follow the dosing instructions provided in the FDA-approved patient labeling.

Table 4: Instructions for Missed MARLISSA® (levonorgestrel and ethinyl estradiol tablets) Tablets

- If one active tablet is missed in Weeks 1, 2, or 3 | Take the tablet as soon as possible. Continue taking one tablet a day until the pack is finished.
- If two active tablets are missed in Week 1 or Week 2 | Take the two missed tablets as soon as possible and the next two active tablets the next day. Continue taking one tablet a day until the pack is finished. Additional nonhormonal contraception (such as condoms or spermicide) should be used as back-up if the patient has sex within 7 days after missing tablets.
- If two active tablets are missed in the third week or three or more active tablets are missed in a row in Weeks 1, 2, or 3 | Day 1 start: Throw out the rest of the pack and start a new pack that same day.; Sunday start: Continue taking one tablet a day until Sunday, then throw out the rest of the pack and start a new pack that same day.; Additional nonhormonal contraception (such as condoms or spermicide) should be used as back-up if the patient has sex within 7 days after missing tablets.

4. Advice in Case of Gastrointestinal Disturbances

If vomiting occurs within 3 to 4 hours after taking MARLISSA® (levonorgestrel and ethinyl estradiol tablets), the patient should proceed as if she missed a tablet. In case of prolonged vomiting or diarrhea, absorption may not be complete and additional contraceptive measures should be taken.

HOW SUPPLIED/ STORAGE AND HANDLING

MARLISSA® (levonorgestrel and ethinyl estradiol tablets, USP 0.15 mg/0.03 mg) is available in cartons (NDC 68462-388- 29) of 3 blisters (NDC 68462-388-84), each containing 28 tablets.

Each blister contains:

21 Active Tablets: Light orange to orange color, round, biconvex, film coated tablets with ‘A5’ debossed on one side.

7 Inert Tablets: Light pink to pink color, round, biconvex, uncoated tablets with ‘A6’ debossed on one side.

Store at 20°C to 25°C (68°F to 77°F); excursions permitted to 15°C to 30°C (59°F to 86°F) [see USP Controlled Room Temperature]. Protect from light.

Distributed by:

Glenmark Pharmaceuticals Inc., USA

Elmwood Park, NJ 07407

Questions? 1 (888) 721-7115

www.glenmarkpharma-us.com

April 2025

Patient Information

MARLISSA® (MĀR-LIS-SĂ)

(Levonorgestrel and Ethinyl Estradiol Tablets, USP 0.15 mg/0.03 mg)

What is the most important information I should know about MARLISSA® (levonorgestrel and ethinyl estradiol tablets)?

Do not use MARLISSA® (levonorgestrel and ethinyl estradiol tablets) if you smoke cigarettes and are over 35 years old. Smoking increases your risk of serious cardiovascular side effects from hormonal birth control pills, including death from heart attack, blood clots or stroke. This risk increases with age and the number of cigarettes you smoke.

What is MARLISSA® (levonorgestrel and ethinyl estradiol tablets)?

MARLISSA® (levonorgestrel and ethinyl estradiol tablets) is a birth control pill (oral contraceptive) used by women to prevent pregnancy.

How does MARLISSA® (levonorgestrel and ethinyl estradiol tablets) work for contraception?

Your chance of getting pregnant depends on how well you follow the directions for taking your birth control pills. The better you follow the directions, the less chance you have of getting pregnant.

Based on the results of clinical studies, about 1 to 5 out of 100 women may get pregnant during the first year they use MARLISSA® (levonorgestrel and ethinyl estradiol tablets).

The following chart shows the chance of getting pregnant for women who use different methods of birth control. Each box on the chart contains a list of birth control methods that are similar in effectiveness. The most effective methods are at the top of the chart. The box on the bottom of the chart shows the chance of getting pregnant for women who do not use birth control and are trying to get pregnant.

Who should not take MARLISSA® (levonorgestrel and ethinyl estradiol tablets)?

Do not take MARLISSA® (levonorgestrel and ethinyl estradiol tablets) if you:

- smoke and are over 35 years of age
- had blood clots in your arms, legs, lungs, or eyes
- had a problem with your blood that makes it clot more than normal
- have certain heart valve problems or irregular heart beat
- had a stroke
- had a heart attack
- have high blood pressure that cannot be controlled by medicine
- have diabetes with kidney, eye, nerve, or blood vessel damage
- have certain kinds of severe migraine headaches with aura, numbness, weakness or changes in vision, or any migraine headaches if you are over 35 years of age
- had breast cancer or any cancer that is sensitive to female hormones
- have liver problems, including liver tumors
- have any unexplained vaginal bleeding
- are pregnant
- take any Hepatitis C drug combination containing ombitasvir/paritaprevir/ritonavir, with or without dasabuvir. This may increase levels of the liver enzyme “alanine aminotransferase” (ALT) in the blood.

If any of these conditions happen while you are taking MARLISSA® (levonorgestrel and ethinyl estradiol tablets), stop taking MARLISSA® (levonorgestrel and ethinyl estradiol tablets) right away and talk to your healthcare provider. Use non-hormonal contraception when you stop taking MARLISSA® (levonorgestrel and ethinyl estradiol tablets).

What should I tell my healthcare provider before taking MARLISSA® (levonorgestrel and ethinyl estradiol tablets)?

Tell your healthcare provider if you:

- are pregnant or think you may be pregnant
- are depressed now or have been depressed in the past
- had yellowing of your skin or eyes (jaundice) caused by pregnancy (cholestasis of pregnancy)
- are breastfeeding or plan to breastfeed. MARLISSA® (levonorgestrel and ethinyl estradiol tablets) may decrease the amount of breast milk you make. A small amount of the hormones in MARLISSA® (levonorgestrel and ethinyl estradiol tablets) may pass into your breast milk. Talk to your healthcare provider about the best birth control method for you while breastfeeding.

Tell your healthcare provider about all the medicines you take, including prescription and over-the-counter medicines, vitamins and herbal supplements.

MARLISSA® (levonorgestrel and ethinyl estradiol tablets) may affect the way other medicines work, and other medicines may affect how well MARLISSA® (levonorgestrel and ethinyl estradiol tablets) works.

Know the medicines you take. Keep a list of them to show your healthcare provider and pharmacist when you get a new medicine.

How should I take MARLISSA® (levonorgestrel and ethinyl estradiol tablets)?

Read the Instructions for Use at the end of this Patient Information.

What are the possible serious side effects of MARLISSA® (levonorgestrel and ethinyl estradiol tablets)?

- Like pregnancy, MARLISSA® (levonorgestrel and ethinyl estradiol tablets) may cause serious side effects, including blood clots in your lungs, heart attack, or a stroke that may lead to death. Some other examples of serious blood clots include blood clots in the legs or eyes.

Serious blood clots can happen especially if you smoke, are obese, or are older than 35 years of age. Serious blood clots are more likely to happen when you:

- first start taking birth control pills
- restart the same or different birth control pills after not using them for a month or more

Call your healthcare provider or go to a hospital emergency room right away if you have:

- leg pain that will not go away

- sudden change in vision or blindness

- sudden severe shortness of breath

- chest pain

- a sudden, severe headache unlike your usual headaches

- weakness or numbness in your arm or leg

- trouble speaking

Other serious side effects include:

- liver problems, including:
  - rare liver tumors
  - jaundice (cholestasis), especially if you previously had cholestasis of pregnancy. Call your healthcare provider if you have yellowing of your skin or eyes.
- high blood pressure. You should see your healthcare provider for a yearly check of your blood pressure.
- gallbladder problems
- changes in the sugar and fat (cholesterol and triglycerides) levels in your blood
- new or worsening headaches, including migraine headaches
- irregular or unusual vaginal bleeding and spotting between your menstrual periods, especially during the first 3 months of taking MARLISSA® (levonorgestrel and ethinyl estradiol tablets).
- depression
- possible cancer in your breast and cervix.
- swelling of your skin especially around your mouth, eyes, and in your throat (angioedema). Call your healthcare provider if you have a swollen face, lips, mouth tongue or throat, which may lead to difficulty swallowing or breathing. Your chance of having angioedema is higher if you have a history of angioedema.
- dark patches of skin around your forehead, nose, cheeks and around your mouth, especially during pregnancy (chloasma). Women who tend to get chloasma should avoid spending a long time in sunlight, tanning booths, and under sun lamps while taking MARLISSA® (levonorgestrel and ethinyl estradiol tablets). Use sunscreen if you have to be in the sunlight.

What are the most common side effects of oral contraceptives?

- nausea

- weight gain

- vomiting

- breast tenderness

- bleeding between menstrual periods

- difficulty wearing contact lenses

These are not all the possible side effects of MARLISSA® (levonorgestrel and ethinyl estradiol tablets). For more information, ask your healthcare provider or pharmacist.

You may report side effects to the FDA at 1-800-FDA-1088.

What else should I know about taking MARLISSA® (levonorgestrel and ethinyl estradiol tablets)?

- If you are scheduled for any lab tests, tell your healthcare provider you are taking MARLISSA® (levonorgestrel and ethinyl estradiol tablets). Certain blood tests may be affected by MARLISSA® (levonorgestrel and ethinyl estradiol tablets).
- MARLISSA® (levonorgestrel and ethinyl estradiol tablets) does not protect against HIV-infection (AIDS) and other sexually transmitted infections.

How should I store MARLISSA® (levonorgestrel and ethinyl estradiol tablets)?

- Store MARLISSA® (levonorgestrel and ethinyl estradiol tablets) at room temperature between 68°F to 77°F (20°C to 25°C).
- Protect from light.

General information about the safe and effective use of MARLISSA® (levonorgestrel and ethinyl estradiol tablets).

Medicines are sometimes prescribed for purposes other than those listed in a Patient Information leaflet. Do not use MARLISSA® (levonorgestrel and ethinyl estradiol tablets) for a condition for which it was not prescribed. Do not give MARLISSA® (levonorgestrel and ethinyl estradiol tablets) to other people, even if they have the same symptoms that you have.

This Patient Information Leaflet summarizes the most important information about MARLISSA® (levonorgestrel and ethinyl estradiol tablets). You can ask your pharmacist or healthcare provider for information about MARLISSA® (levonorgestrel and ethinyl estradiol tablets) that is written for health professionals.

For more information, call 1 (888) 721-7115.

Do birth control cause cancer?

There may be slight increases in the risk of breast cancer among current users of hormonal birth control pills with longer duration of use of 8 years or more.

Women who use birth control pills may have a slightly higher chance of getting cervical cancer. However, this may be due to other reasons such as having more sexual partners.

What if I want to become pregnant?

You may stop taking the pill whenever you wish. Consider a visit with your healthcare provider for a pre-pregnancy checkup before you stop taking the pill.

What should I know about my period when taking MARLISSA® (levonorgestrel and ethinyl estradiol tablets)?

Your periods may be lighter and shorter than usual. Some women may miss a period. Irregular vaginal bleeding or spotting may happen while you are taking MARLISSA® (levonorgestrel and ethinyl estradiol tablets), especially during the first few months of use. This usually is not a serious problem. It is important to continue taking your pills on a regular schedule to prevent a pregnancy.

What are the ingredients in MARLISSA® (levonorgestrel and ethinyl estradiol tablets)?

Active ingredients: Each light orange to orange pill contains levonorgestrel and ethinyl estradiol.

Inactive ingredients:

Light orange to orange pills: FD&C Yellow no. 6, lactose monohydrate, magnesium stearate, microcrystalline cellulose, polacrilin potassium, povidone and talc. In addition, the film-coating contains hypromellose and macrogol.

Light pink to pink inert tablets: D&C Red no. 30, lactose monohydrate, magnesium stearate, microcrystalline cellulose, polacrilin potassium, povidone and talc.

Distributed by:

Glenmark Pharmaceuticals Inc., USA

Elmwood Park, NJ 07407

Questions? 1 (888) 721-7115

www.glenmarkpharma-us.com

April 2025

Instructions For Use

MARLISSA® (MĀR-LIS-SĂ)

(Levonorgestrel and Ethinyl Estradiol Tablets, USP 0.15 mg/0.03 mg)

Important Information about taking MARLISSA® (levonorgestrel and ethinyl estradiol tablets)

- Take 1 pill every day at the same time. Take the pills in the order directed on your pill pack.
- Do not skip your pills, even if you do not have sex often. If you miss pills (including starting the pack late) you could get pregnant. The more pills you miss, the more likely you are to get pregnant.
- If you have trouble remembering to take MARLISSA® (levonorgestrel and ethinyl estradiol tablets), talk to your healthcare provider.
- When you first start taking MARLISSA® (levonorgestrel and ethinyl estradiol tablets), spotting or light bleeding in between your periods may occur. Contact your healthcare provider if this does not go away after a few months.
- You may feel sick to your stomach (nauseous), especially during the first few months of taking MARLISSA® (levonorgestrel and ethinyl estradiol tablets). If you feel sick to your stomach, do not stop taking the pill. The problem will usually go away. If your nausea does not go away, call your healthcare provider.
- Missing pills can also cause spotting or light bleeding, even when you take the missed pills later. On the days you take 2 pills to make up for missed pills (see What should I do if I miss any MARLISSA® (levonorgestrel and ethinyl estradiol tablets) pills? below), you could also feel a little sick to your stomach.
- It is not uncommon to miss a period. However, if you miss a period and have not taken MARLISSA® (levonorgestrel and ethinyl estradiol tablets) according to directions, or feel like you may be pregnant, call your healthcare provider. If you have a positive pregnancy test, you should stop taking MARLISSA® (levonorgestrel and ethinyl estradiol tablets).
- If you have vomiting or diarrhea within 3-4 hours of taking a light orange pill, take another light orange pill as soon as possible. Continue taking all your remaining pills in order. Start the first pill of your next pill pack the day after finishing your current pill pack. This will be 1 day earlier than originally scheduled. Continue on your new schedule.
- If you have vomiting or diarrhea for more than 1 day, your birth control pills may not work as well. Use an additional birth control method, like condoms or spermicide, until you check with your healthcare provider.
- Stop taking MARLISSA® (levonorgestrel and ethinyl estradiol tablets) at least 4 weeks before you have major surgery and do not restart after the surgery without asking your healthcare provider. Be sure to use other forms of contraception (like condoms or spermicide) during this time period.

Before you start taking MARLISSA® (levonorgestrel and ethinyl estradiol tablets):

- Decide what time of day you want to take your pill. It is important to take it at the same time every day and in the order as directed on your pill pack.
- Look at your pill pack. Your pill pack consists of 1 blister that holds 28 individually sealed pills. The 28 pills consist of 21 light orange to orange pills (3 rows of 7 pills) and 7 light pink to pink pills (1 row of 7 pills). See Figure A.

- Also find:
  - Where on the blister to start taking pills (upper left corner) and
  - In what order to take the pills (follow the weeks)
- Be sure you have ready at all times another kind of birth control (such as condoms or spermicide), to use as a back-up in case you miss pills.

When should I start taking MARLISSA® (levonorgestrel and ethinyl estradiol tablets)?

If you start taking MARLISSA® (levonorgestrel and ethinyl estradiol tablets) and you have not used a hormonal birth control method before:

- There are 2 ways to start taking your birth control pills. You can either start on a Sunday (Sunday Start) or on the first day (Day 1) of your natural menstrual period (Day 1 Start). Your healthcare provider should tell you when to start taking your birth control pill.
- If you use the Sunday Start, use non-hormonal back-up contraception such as condoms or spermicide for the first 7 days that you take MARLISSA® (levonorgestrel and ethinyl estradiol tablets). You do not need back-up contraception if you use the Day 1 Start.

If you start taking MARLISSA® (levonorgestrel and ethinyl estradiol tablets) and you are switching from another birth control pill:

- Start your new MARLISSA® (levonorgestrel and ethinyl estradiol tablets) pack on the same day that you would start the next pack of your previous birth control method.
- Do not continue taking the pills from your previous birth control pill pack.

If you start taking MARLISSA® (levonorgestrel and ethinyl estradiol tablets) and previously used a vaginal ring:

- Start using MARLISSA® (levonorgestrel and ethinyl estradiol tablets) on the day you would have started the next ring.

If you start taking MARLISSA® (levonorgestrel and ethinyl estradiol tablets) and previously used a transdermal patch:

- Start using MARLISSA® (levonorgestrel and ethinyl estradiol tablets) on the day you would have started a new cycle (first patch application).

If you start taking MARLISSA® (levonorgestrel and ethinyl estradiol tablets) and you are switching from a progestin-only method such as an implant or injection:

- Start taking MARLISSA® (levonorgestrel and ethinyl estradiol tablets) on the day of removal of your implant, or on the day when you would have had your next injection.

If you start taking MARLISSA® (levonorgestrel and ethinyl estradiol tablets) and you are switching from an intrauterine device or system (IUD or IUS):

- Start taking MARLISSA® (levonorgestrel and ethinyl estradiol tablets) on the day of removal of your IUD or IUS.
- You do not need back-up contraception if your IUD or IUS is removed on the first day (Day 1) of your period. If your IUD or IUS is removed on any other day, use non-hormonal back-up contraception such as condoms or spermicide for the first 7 days that you take MARLISSA® (levonorgestrel and ethinyl estradiol tablets).

Keep a calendar to track your period: If this is the first time you are taking birth control pills, read, “When should I start taking MARLISSA® (levonorgestrel and ethinyl estradiol tablets)?” above. Follow these instructions for either a Sunday Start or a Day 1 Start.

Instructions for using your MARLISSA® (levonorgestrel and ethinyl estradiol tablets) Pill Dispenser:

Sunday Start:

You will use a Sunday Start if your healthcare provider told you to take your first pill on a Sunday.

- Take pill 1 on the Sunday after your period starts. To remove your pill from the dispenser, press the pill through the hole in the bottom of the dispenser.
- If your period starts on a Sunday, take pill "1" that day and refer to Day 1 Start instructions below.
- Take 1 pill every day in the order on the pill dispenser at the same time each day for 28 days.
- After taking the last pill on Day 28 from the pill dispenser, start taking the first pill from a new pack, on the same day of the week as the first pack (Sunday). Take the first pill in the new pack whether or not you are having your period.
- Use non-hormonal back-up contraception such as condoms or spermicide for the first 7 days of the first cycle that you take MARLISSA® (levonorgestrel and ethinyl estradiol tablets).

Day 1 Start:

You will use a Day 1 Start if your doctor told you to take your first pill (Day 1) on the first day of your period.

- Take 1 pill every day in the order of the pill dispenser, at the same time each day, for 28 days. To remove your pill from the dispenser, press the pill through the hole in the bottom of the dispenser.
- After taking the last pill on Day 28 from the pill dispenser, start taking the first pill from a new pack, on the same day of the week as the first pack. Take the first pill in the new pack whether or not you are having your period.

What should I do if I miss any MARLISSA® (levonorgestrel and ethinyl estradiol tablets) pills?

If you miss 1 pill in Weeks 1, 2, or 3, follow these steps:

- Take it as soon as you remember. Take the next pill at your regular time. This means you may take 2 pills in 1 day.
- Then continue taking 1 pill every day until you finish the pack.
- You do not need to use a back-up birth control method if you have sex.

If you miss 2 pills in Week 1 or Week 2 of your pack, follow these steps:

- Take the 2 missed pills as soon as possible and the next 2 pills the next day.
- Then continue to take 1 pill every day until you finish the pack.
- Use a non-hormonal birth control method (such as a condom or spermicide) as a back-up if you have sex during the first 7 days after missing your pills.

If you miss 2 pills in a row in Week 3, or you miss 3 or more pills in a row during Weeks 1, 2, or 3 of the pack, follow these steps:

- If you are a Day 1 Starter:
  - Throw out the rest of the pill pack and start a new pack that same day.
  - You may not have your period this month, but this is expected. However, if you miss your period 2 months in a row, call your healthcare provider because you might be pregnant.
  - You could become pregnant if you have sex during the first 7 days after you restart your pills. You MUST use a non-hormonal birth control method (such as a condom or spermicide) as a back-up if you have sex during the first 7 days after you restart your pills.
- If you are a Sunday Starter:
  - Keep taking 1 pill every day until Sunday. On Sunday, throw out the rest of the pack and start a new pack of pills that same day.
  - Use a non-hormonal birth control method (such as a condom or spermicide) as a back-up if you have sex during the first 7 days after you restart your pills.

If you have any questions or are unsure about the information in this leaflet, call your healthcare provider.

This Patient Information and Instructions for Use have been approved by the U.S. Food and Drug Administration.

Distributed by:

Glenmark Pharmaceuticals Inc., USA

Elmwood Park, NJ 07407

Questions? 1 (888) 721-7115

www.glenmarkpharma-us.com

April 2025